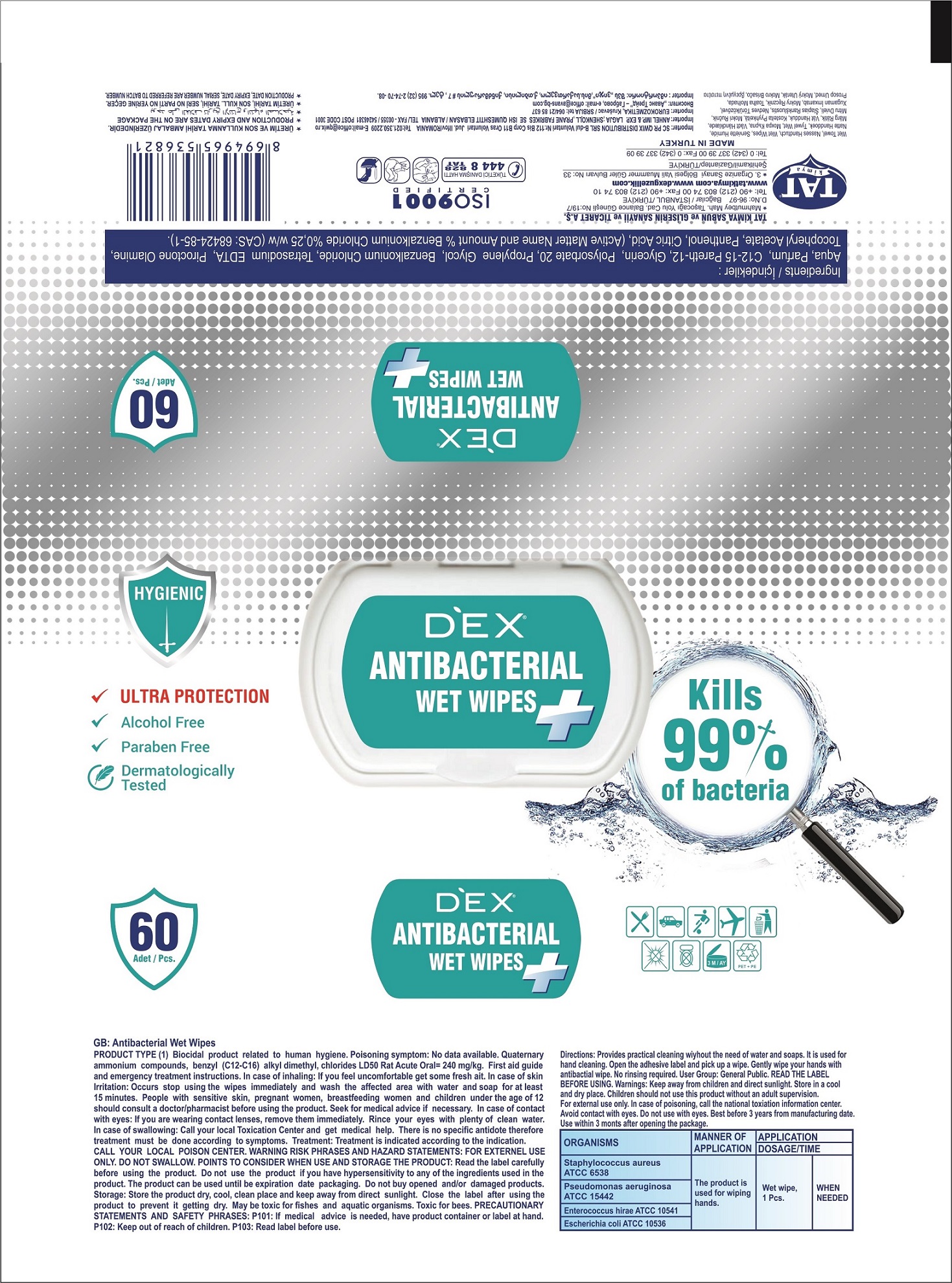 DRUG LABEL: Dex Antibacterial Wipes
NDC: 78141-800 | Form: CLOTH
Manufacturer: Fuson LLC
Category: otc | Type: HUMAN OTC DRUG LABEL
Date: 20200704

ACTIVE INGREDIENTS: BENZALKONIUM CHLORIDE 0.13 g/100 g
INACTIVE INGREDIENTS: C12-15 PARETH-12; PIROCTONE OLAMINE; EDETATE SODIUM; PANTHENOL; .ALPHA.-TOCOPHEROL ACETATE; POLYSORBATE 20; GLYCERIN; WATER; CITRIC ACID MONOHYDRATE; PROPYLENE GLYCOL

Active Ingredient

Benzalkonium Chloride .13% v/v. Purpose: Antiseptic

Purpose

Antiseptic, Antibacterial Wet Hand Wipes

Use

Antibacterial wet wipes helps reduce bacteria (organisms).Effective on bacterias :Staphylococcus aureus ATCC 6538,Pseudomonas aeruginosa ATCC 15442,Enterococcus hirae ATCC 10541,Escherichia coli ATCC 10536. Use only on hands and away from eyes.

Warnings

Keep away from children and direct sunlight. Children should not use this product without an adult supervision. For external use only. In case of poisoning, call the National Toxitation Information Center. Avoid contact with eyes. This product consists of nonwoven fabric (solid) impregnated with a flammable liquid solution that has an estimated flashpoint of approximately 120 degrees fahrenheit; keep away from heat, sparks, open flames, and hot surfaces. Do not smoke near this product or while using. Keep container tightly closed when not in use.

Do not use if allergic to any of its ingredients. Do not use near eyes. Consult a doctor before use if pregnant, breastfeeding, have sensitive skin, or are under the age of 12. Do not buy opened and/or damaged products.

When Using

In case of inhaling: If you feel uncomfortable get some fresh air. In case of skin Irritation: Occurs stop using the wipes immediately and wash the affected area with water and soap for at least 15 minutes. People with sensitive skin, pregnant women, breastfeeding women and children under the age of 12 should consult a doctor/pharmacist before using the product. Seek for medical advice if necessary. In case of contact with eyes: If you are wearing contact lenses, remove them immediately. Rince your eyes with plenty of clean water. In case of swallowing: Call your local Toxication Center and get medical help.

Stop Using

Stop use if rednedd or irritation occurs and persists for longer than 48 hours and contact a healthcare professional.

KEEP OUT OF REACH OF CHILDREN

Keep away from children. Children should not use this product without adult supervision.

Directions

Provides practical cleaning without need of water and soap. Used for hand cleaning. Open the adhesive label and pick up a wipe. Gently wipe your hands with antibacterial wipe. No rinsing required.

Other Information

Do not ingest the product internally. Store in a cool, dry place. Store away from oxidizing agents and food.

Inactive Ingredients

Aqua, Parfum, C12-15 Pareth-12, Glycerin, Polysorbate 20, Propylene Glycol, Tetrasodium EDTA, Piroctone Olamine, Tocopheryl Acetate, Panthenol, Citric Acid

Indications and Usage; Dosage and Administration

Indications and Usage section was added

Dosage and Administration section was added